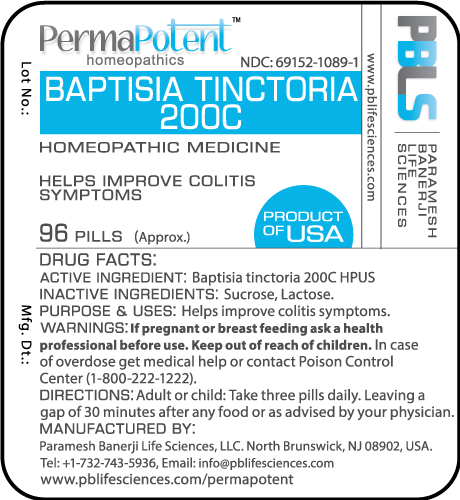 DRUG LABEL: Baptisia tinctoria 200C
NDC: 69152-1089 | Form: PELLET
Manufacturer: Paramesh Banerji Life Sciences LLC
Category: homeopathic | Type: HUMAN OTC DRUG LABEL
Date: 20170207

ACTIVE INGREDIENTS: BAPTISIA TINCTORIA ROOT 200 [hp_C]/1 1
INACTIVE INGREDIENTS: LACTOSE; SUCROSE

DRUG FACTS: Active Ingredient

Baptisia tinctoria 200C HPUS

Inactive Ingredients

Sucrose, Lactose

Purpose

Helps improve colitis symptoms

Uses

Helps improve colitis symptoms

Warnings

If pregnant or breast feeding ask a health professional before use.

Keep out of reach of children. In case of overdose, get medical help or contact a Poison Control Center (1-800-222-1222) right away.

Direction

Adult or child: Take three pills daily. Leaving a gap of 30 minutes after any food or as advised by your physician.

Manufactured by

Paramesh Banerji Life Sciences, LLC.

North Brunswick, NJ 08902, USA.

Tel: +1-732-743-5936,

Email: info@pblifesciences.com

www.pblifesciences.com/permapotent

Principal Display Panel

NDC: 69152-1089-1

Baptisia tinctoria 200C

Homeopathic Medicine

Helps improve colitis symptoms

96 Pills (Approx.)

Product of USA